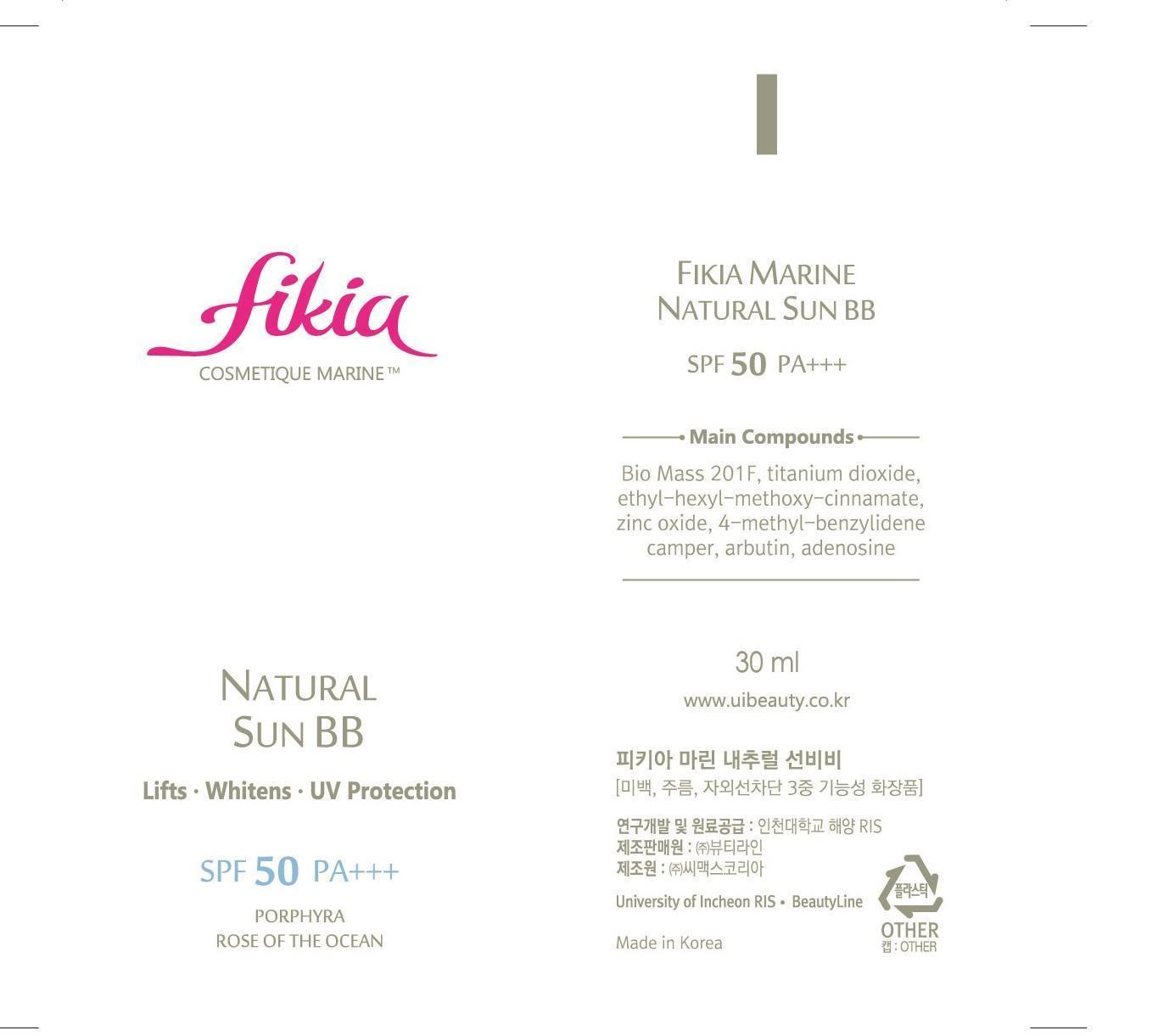 DRUG LABEL: Fikia Marine Natural Sun BB SPF 50 PA
NDC: 69327-4001 | Form: CREAM
Manufacturer: Beauty Line Co., Ltd.
Category: otc | Type: HUMAN OTC DRUG LABEL
Date: 20141025

ACTIVE INGREDIENTS: TITANIUM DIOXIDE 7.5 g/100 mL
INACTIVE INGREDIENTS: WATER; BUTYLENE GLYCOL; SODIUM CHLORIDE

Drug Facts

ACTIVE INGREDIENT

titanium dioxide

INACTIVE INGREDIENT

water, glycerin, zinc oxide, dimethicone, porphyra tenera ext, butylene glycol, arbutin, sodium chloride, iron dioxide, etc

PURPOSE

whitening
anti-wrinkle
sun block

keep out or reach of the children

INDICATIONS AND USAGE

apply evenly after daily skin-care routine

WARNINGS

-If in contact with the eyes, wash out thoroughty with water If the symptoms are servere, seek medical advice immediately
-This product is for exeternal use only. Do not use for internal use
-If possible, avoid direct sunlight and store in cool and area of low humidity
-In order to maintain the quality of the product and avoid misuse
-Avoid placing the product near fire and store out in reach of children

DOSAGE AND ADMINISTRATION

for external use only